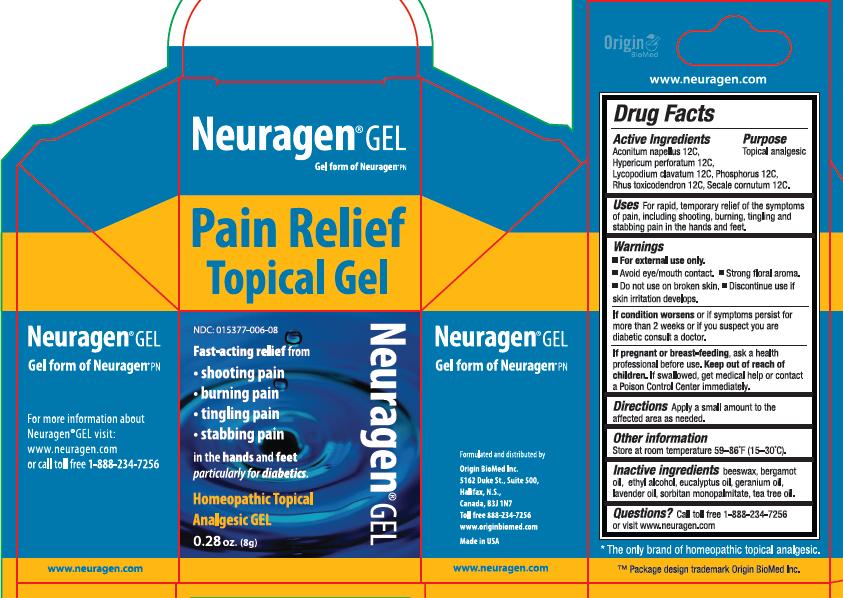 DRUG LABEL: Neuragen
NDC: 15377-006 | Form: GEL
Manufacturer: Origin Biomed Inc
Category: homeopathic | Type: HUMAN OTC DRUG LABEL
Date: 20110816

ACTIVE INGREDIENTS: HYPERICUM PERFORATUM 12 [hp_C]/8 g; ACONITUM NAPELLUS 12 [hp_C]/8 g; LYCOPODIUM CLAVATUM SPORE 12 [hp_C]/8 g; PHOSPHORUS 12 [hp_C]/8 g; TOXICODENDRON PUBESCENS LEAF 12 [hp_C]/8 g; CLAVICEPS PURPUREA SCLEROTIUM 12 [hp_C]/8 g
INACTIVE INGREDIENTS: BERGAMOT OIL; ALCOHOL; EUCALYPTUS OIL; GERANIUM OIL, ALGERIAN TYPE; LAVENDER OIL; TEA TREE OIL

INACTIVE INGREDIENT

bergamot oil, beeswax, ethyl alcohol, eucalyptus oil, geranium oil, lavender oil, sorbitan monopalmitate, tea tree oil

DOSAGE AND ADMINISTRATION

Apply a small amount to the affected area as needed.

WARNINGS

- For external use only.
- Avoid eye/mouth contact
- Strong floral aroma
- Do not use on broken skin.
- Discontinue use if skin irritation develops

If condition worsens or if symptoms persist for more than 2 weeks or if you suspect you are diabetic consult a doctor.

ACTIVE INGREDIENT

Aconitum Napellus 12 C, Hypericum perforatum 12 C, Lycopodium clavatum 12 C, Phosphorus 12 C, Rhus toxicodendron 12 C, Secale cornutum 12 C

PURPOSE

Topical analgesic

PREGNANCY OR BREAST FEEDING

If pregnant or breast feeding, ask a health professional before use.

Keep out of reach of children. If swallowed, get medical help or contact a Poison Control Center immediately.

INDICATIONS AND USAGE

For rapid, temporary relief of the symptoms of pain, including shooting, burning, tingling and stabbing pain in the hands and feet.

STORAGE AND HANDLING

Store at room temperature 59-86 degrees F (15-30 degrees C)

QUESTIONS

Call toll free 1-888-234-7256 or visit www.neuragen.com